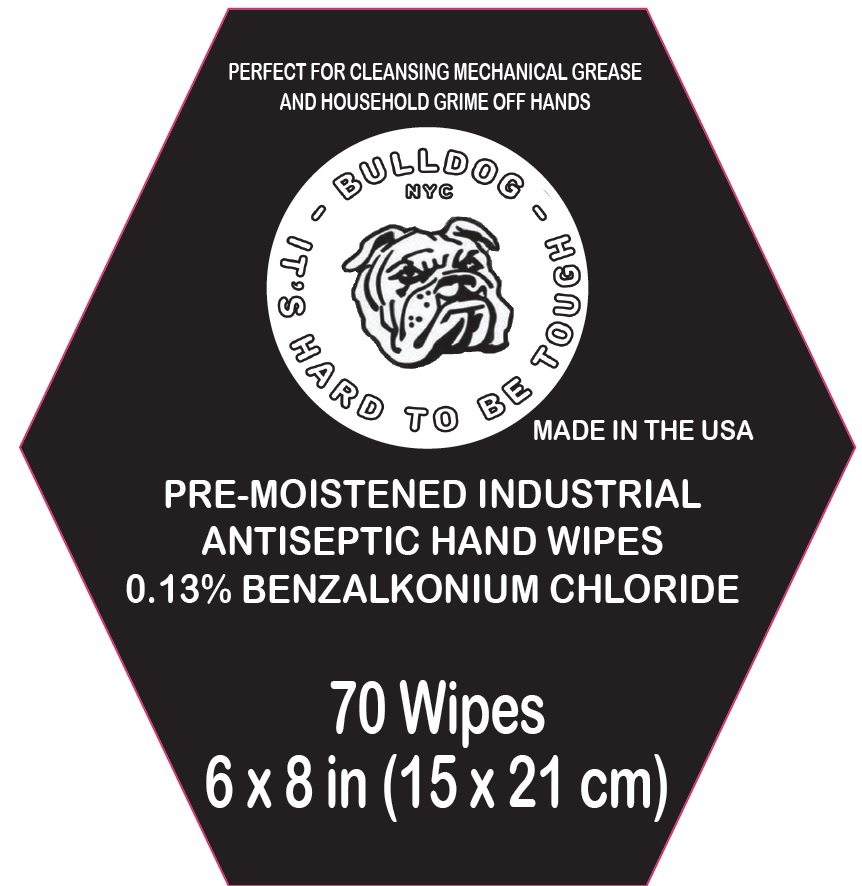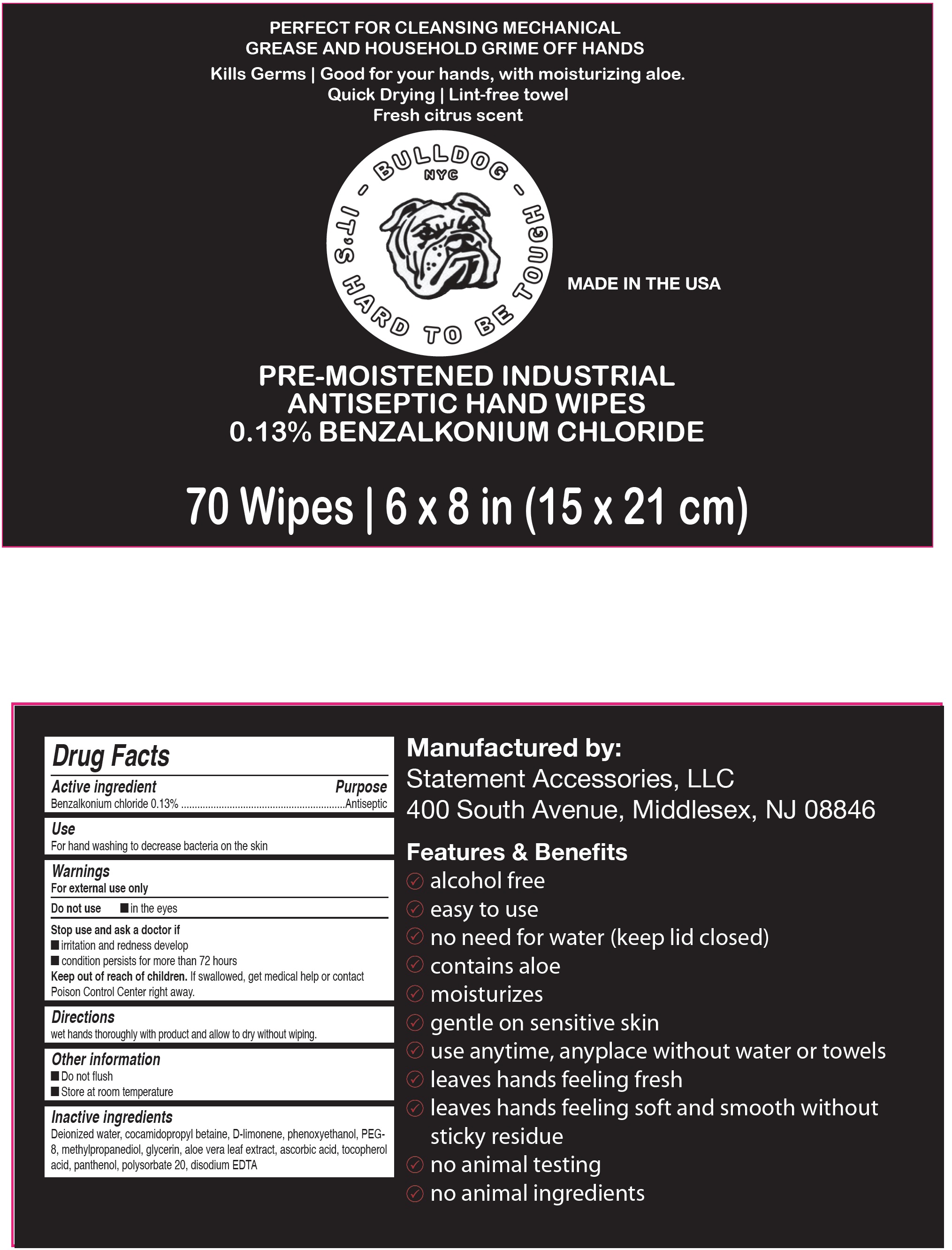 DRUG LABEL: Bulldog NYC Pre-Moistened Industrial Antiseptic Hand Wipes
NDC: 80249-001 | Form: CLOTH
Manufacturer: STATEMENT ACCESSORIES LLC
Category: otc | Type: HUMAN OTC DRUG LABEL
Date: 20200831

ACTIVE INGREDIENTS: BENZALKONIUM CHLORIDE 1.3 mg/1 mL
INACTIVE INGREDIENTS: WATER; COCAMIDOPROPYL BETAINE; LIMONENE, (+)-; PHENOXYETHANOL; POLYETHYLENE GLYCOL 400; METHYLPROPANEDIOL; ALOE VERA LEAF; ASCORBIC ACID; TOCOPHEROL; PANTHENOL; POLYSORBATE 20; EDETATE DISODIUM ANHYDROUS; GLYCERIN

Bulldog NYC Pre-Moistened Industrial Antiseptic Hand Wipes

Active ingredient

Benzalkonium chloride 0.13%

Purpose

Antiseptic

Use

For hand washing to decrease bacteria on the skin

Warnings

For external use only

Do not use

- in the eyes

Stop use and ask a doctor if

- irritation and redness develop
- condition persists for more than 72 hours

Keep out of reach of children.

If swallowed, get medical help or contact Poison Control Center right away.

Directions:

wet hands thoroughly with product and allow to dry without wiping.

Other information

- Do not flush
- Store at room temperature

Inactive ingredients

Deionized water, cocamidopropyl betaine, D-limonene, phenoxyethanol, Peg-8, methylpropanediol, aloe vera leaf extract, ascorbic acid, tocopherol acid, panthenol, polysorbate 20, disodium EDTA